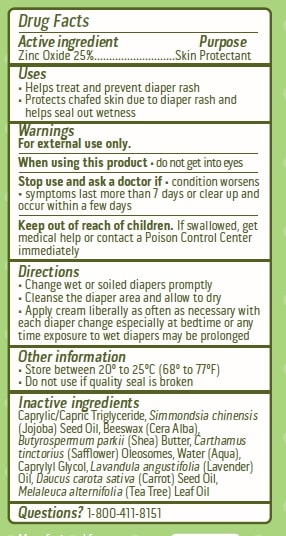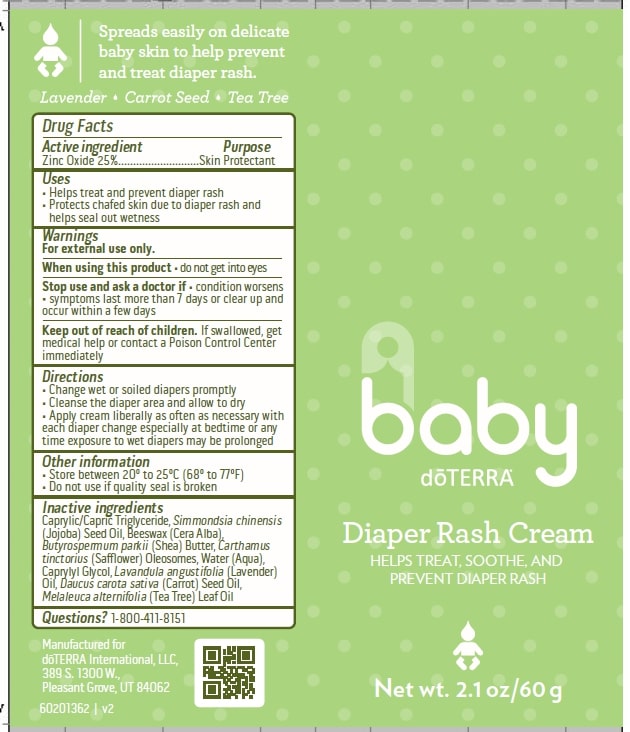 DRUG LABEL: Baby Diaper Rash Cream
NDC: 71630-549 | Form: CREAM
Manufacturer: doTERRA International, LLC
Category: otc | Type: HUMAN OTC DRUG LABEL
Date: 20250128

ACTIVE INGREDIENTS: ZINC OXIDE 25 g/100 g
INACTIVE INGREDIENTS: WATER; MEDIUM-CHAIN TRIGLYCERIDES; JOJOBA OIL; CARROT SEED OIL; YELLOW WAX; CAPRYLYL GLYCOL; LAVENDER OIL; TEA TREE OIL; CARTHAMUS TINCTORIUS (SAFFLOWER) OLEOSOMES; SHEA BUTTER

Baby Diaper Rash Cream

ACTIVE INGREDIENT

Zinc Oxide 25%

PURPOSE

Skin protectant

Uses

• Helps treat and prevent diaper rash
• Protects chafed skin due to diaper rash and
helps seal out wetness

WARNINGS

For external use only.

When using this product do not get into eyes

Stop use and ask a doctor if • condition worsens
• symptoms last more than 7 days or clear up and
occur again within a few days

Keep out of reach of children. If swallowed, get medical help or contact a Poison Control Center immediately.

Other information

• Store between 20º to 25ºC (68º to 77ºF)
• Do not use if quality seal is broken

INACTIVE INGREDIENT

Inactive ingredients: Caprylic/Capric Triglyceride, Simmondsia chinensis
(Jojoba) Seed Oil, Beeswax (Cera Alba),
Butyrospermum parkii (Shea) Butter, Carthamus
tinctorius (Safflower) Oleosomes, Water (Aqua),
Caprylyl Glycol, Lavandula angustifolia (Lavender)
Oil, Daucus carota sativa (Carrot) Seed Oil,
Melaleuca alternifolia (Tea Tree) Leaf Oil

Questions? Call 1-800-411-8151

Active ingredient Purpose

Zinc Oxide 25%...........................Skin Protectant

Directions

• Change wet or soiled diapers promptly
• Cleanse the diaper area and allow to dry
• Apply cream liberally as often as necessary with
each diaper change especially at bedtime or any
time exposure to wet diapers may be prolonged

Principal Display Panel and Package Label

doTERRA® baby

Diaper Rash Cream

Helps Treat, Soothe, and Prevent Diaper Rash

Net wt. 2.1 oz/60 g